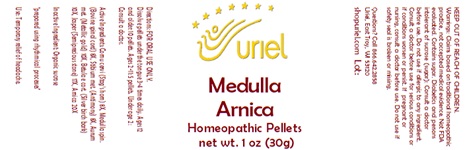 DRUG LABEL: Medulla Arnica
NDC: 48951-7022 | Form: PELLET
Manufacturer: Uriel Pharmacy Inc.
Category: homeopathic | Type: HUMAN OTC DRUG LABEL
Date: 20240205

ACTIVE INGREDIENTS: CERVUS ELAPHUS WHOLE 8 [hp_X]/1 1; BOS TAURUS SPINAL CORD 8 [hp_X]/1 1; ANTIMONY 8 [hp_X]/1 1; GOLD 10 [hp_X]/1 1; BETULA PUBESCENS BARK 10 [hp_X]/1 1; SILICON DIOXIDE 17 [hp_X]/1 1; ARNICA MONTANA 20 [hp_X]/1 1
INACTIVE INGREDIENTS: SUCROSE

Medulla Arnica

INDICATIONS AND USAGE

Directions: FOR ORAL USE ONLY.

DOSAGE AND ADMINISTRATION

Dissolve pellets under the tongue 3-4 times daily. Ages 12 and older: 10 pellets. Ages 2-11: 5 pellets. Under age 2: Consult a doctor.

ACTIVE INGREDIENT

Active Ingredients: Cornu cervi (Stag’s horn) 8X, Medulla spin. (Bovine spinal cord) 8X, Stibium met. (Antimony) 8X, Aurum met. (Metallic gold) 10X, Betula e cort. (Silver birch bark) 10X, Jasper (Semiprecious stone) 17X, Arnica 20X

Inactive Ingredient: Organic sucrose

"prepared using rhythmical processes"

PURPOSE

Use: Temporary relief of headache.

KEEP OUT OF REACH OF CHILDREN.

WARNINGS

Warnings: Claims based on traditional homeopathic practice, not accepted medical evidence. Not FDA evaluated. Contains sugar. Diabetics and persons intolerant of sucrose (sugar): Consult a doctor before use. Do not use if allergic to any ingredient. Consult a doctor before use for serious conditions or if conditions worsen or persist. If pregnant or nursing, consult a doctor before use. Do not use if safety seal is broken or missing.

QUESTIONS

Questions? Call 866.642.2858 Uriel, East Troy, WI 53120 shopuriel.com Lot: